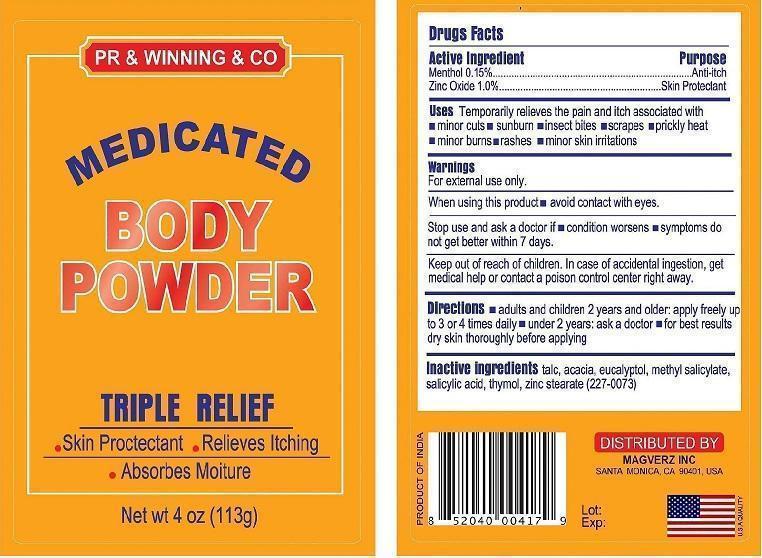 DRUG LABEL: Medicated Body Powder
NDC: 59240-001 | Form: POWDER
Manufacturer: MAGVERZ INC
Category: otc | Type: HUMAN OTC DRUG LABEL
Date: 20130715

ACTIVE INGREDIENTS: MENTHOL 0.15 g/100 g; ZINC OXIDE 1 g/100 g
INACTIVE INGREDIENTS: TALC; Salicylic Acid; ACACIA; EUCALYPTOL; METHYL SALICYLATE; THYMOL; ZINC STEARATE

Medicated Powder

Acitves

Menthol 0.15%
Zinc Oxide 1.0%

Inactives

Talc
Salicylic Acid
Methyl Salicylate
Eucalyptol
Thymol
Zinc Stearate

Acacia

Uses

Temporarily relieves the pain and itch associated with

Minor cuts

- Sunburn Insect Bites
- Scrapes Prickly
- HeatMinor
- Burns Rashes
- Minor Skin Irritations

Purpose

Temporarily relieves the pain and itch

Directions

- Adults and children 2 years and older apply freely up to 3 or 4 times daily.
- Children under 2 years ask a doctor.
- For best results dry skin thoroughly before applying.

Warning

For external use only.

When using this product avoid contact with eyes.

Stop use and ask doctor if condition worsens, symptomos do not get better within 7 days.

Keep Out of Reach of Childrens